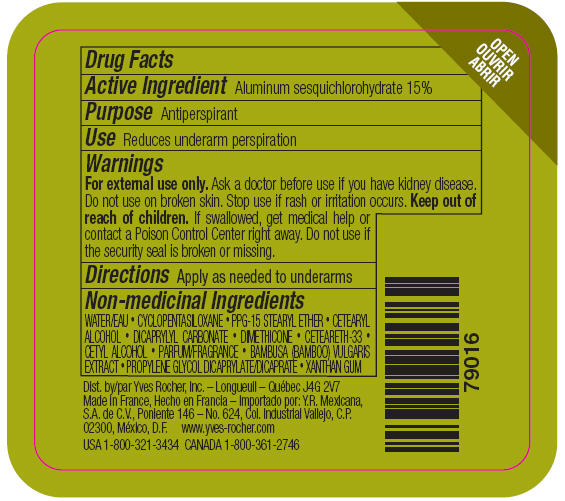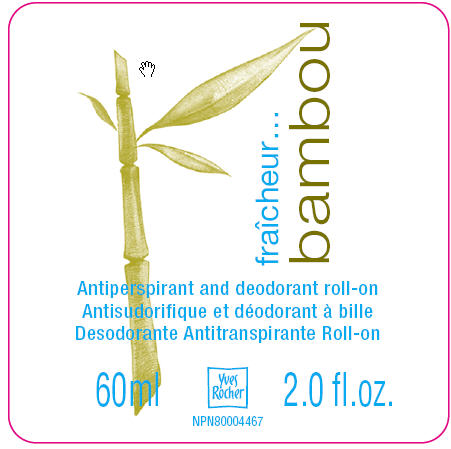 DRUG LABEL: FRAICHEUR BAMBOU ANTIPERSPIRANT AND DEODORANT ROLL-ON
NDC: 54235-208 | Form: LOTION
Manufacturer: Yves Rocher North America Inc. DBA Laboratoire de biologie vegetal Yves Rocher
Category: otc | Type: HUMAN OTC DRUG LABEL
Date: 20110331

ACTIVE INGREDIENTS: ALUMINUM SESQUICHLOROHYDRATE 15 mL/100 mL
INACTIVE INGREDIENTS: WATER 64.1923 mL/100 mL; CYCLOMETHICONE 5 8.0 mL/100 mL; ETHER 4 mL/100 mL; CETOSTEARYL ALCOHOL 3.2 mL/100 mL; DICAPRYLYL CARBONATE 2 mL/100 mL; DIMETHICONE 2 mL/100 mL; CETEARETH-33 0.8 mL/100 mL; CETYL ALCOHOL 0.5 mL/100 mL; PROPYLENE GLYCOL DICAPRYLATE/DICAPRATE 0.0042 mL/100 mL; BAMBUSA VULGARIS TOP  0.0032 mL/100 mL; XANTHAN GUM 0.0003 mL/100 mL

Active ingredient
Aluminum sesquichlorohydrate 15%

Purpose
Antiperspirant

Keep out of reach of children. If swallowed, get medical help or contact a Poison Control Center right away.

Use
Reduces underarm perspiration

Warnings:
For external use only. Ask a doctor before use if you have kidney disease. Do not use on broken skin. Stop use if rash or irritation occurs.

Directions:
Apply as needed to underarms

INACTIVE INGREDIENT

Non-medicinal ingredients: WATER • CYCLOPENTASILOXANE • PPG-15 STEARYL ETHER • CETEARYL ALCOHOL • DICAPRYLYL CARBONATE • DIMETHICONE • CETEARETH-33 • CETYL ALCOHOL • FRAGRANCE • BAMBUSA (BAMBOO) VULGARIS EXTRACT • PROPYLENE GLYCOL DICAPRYLATE/DICAPRATE •XANTHAN GUM

PACKAGE LABEL

Fraicheur bambou
Antiperspirant and deodorant roll-on
60 ml - 2.0 fl. oz.